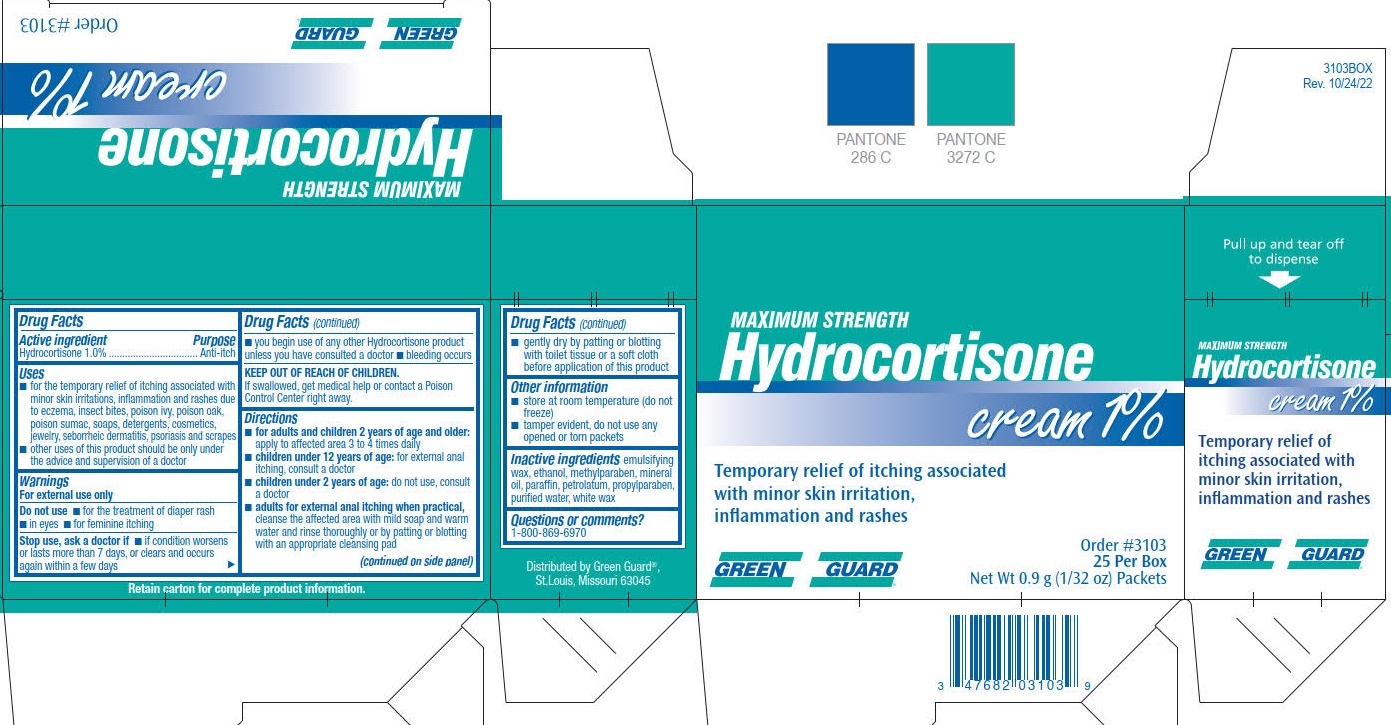 DRUG LABEL: Hydrocortisone
NDC: 47682-397 | Form: CREAM
Manufacturer: Unifirst First Aid Corporation
Category: otc | Type: HUMAN OTC DRUG LABEL
Date: 20250908

ACTIVE INGREDIENTS: HYDROCORTISONE 10 mg/1 g
INACTIVE INGREDIENTS: METHYLPARABEN; ALCOHOL; MINERAL OIL; PARAFFIN; PETROLATUM; PROPYLPARABEN; WATER; WHITE WAX

Green Guard Maximum Strength Hydrocortisone Cream 1%

Drug Facts

Active ingredient

Hydrocortisone 1.0%

Purpose

Anti itch

Uses

- for the temporary relief of itching associated with minor skin irritations, inflammation and rashes
- for external genital, feminine and anal itching
- other uses of this product should be only under the advice and supervision of a doctor

Warnings

For external use only

Do not use

- for the treatment of diaper rash
- in eyes
- for feminine itching

Stop use and ask a doctor if

- condition worsens or lasts more than 7 days, or clears and occurs again within a few days
- you begin use of any other Hydrocortisone product unless you have consulted a doctor
- bleeding occurs

Keep out of reach of children

If swallowed, get medical help or contact a Poison Control Center right away.

Directions

- for adults and children (2 years of age and older): apply to affected area 3 to 4 times daily
- children under 12 years of age: for external anal itching, consult a doctor
- children under 2 years of age: do not use, consult a doctor
- adults for external anal itching when practical, cleanse the affected area with mild soap and warm water and rinse thoroughly or by patting or blotting with an appropriate cleansing pad
- gently dry by patting or botting with toilet tissue or a soft cloth before application of this product

Other information

- store at room temperature (do not freeze)
- tamper evident, do not use any opened or torn packets

Questions or comments?

1-800-869-6970

Inactive ingredient

emulsifying wax, ethanoll, methylparaben, mineral oil, paraffin, petrolatum, propylparaben, purified water, white wax

Green Guard Hydrocortisone Label

Maximum Strength

Hydrocortisone
cream 1%

Temporary relief of itching associated with minor skin irritation, inflammation and rashes

Green Guard

Order # 3103

25 Per Box

Net Wt 0.9 g (1/32 oz) Packets